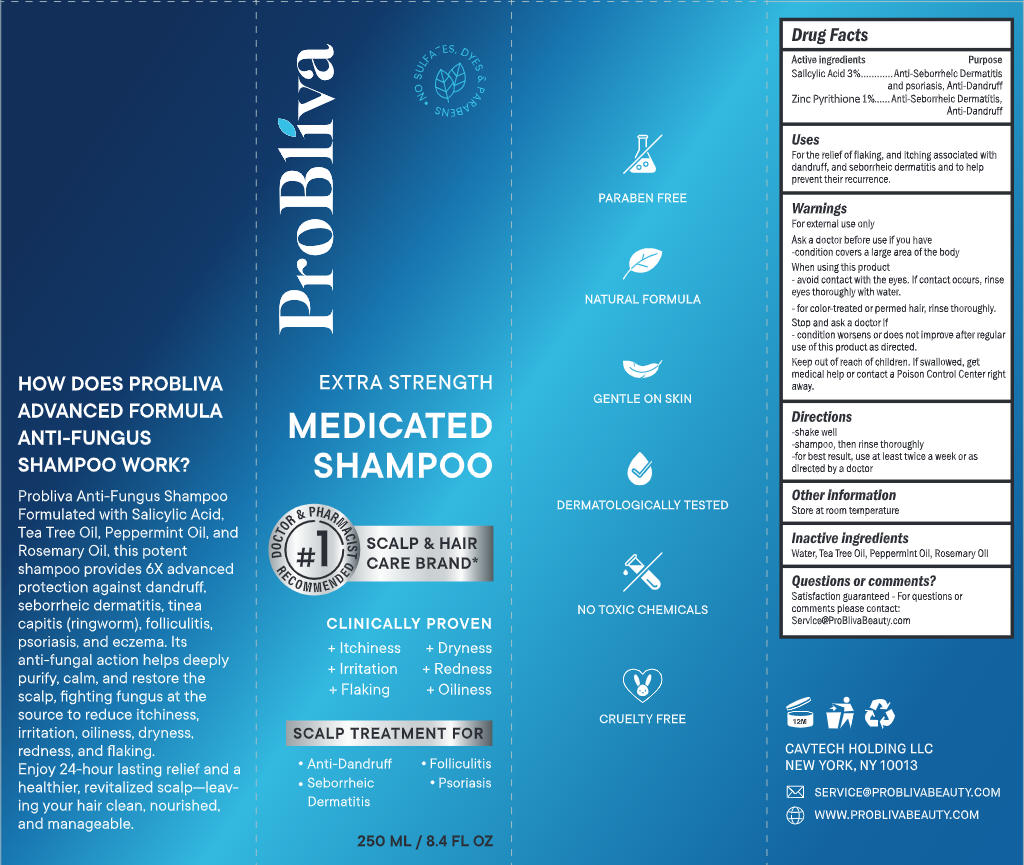 DRUG LABEL: ProBliva Medicated Anti Fungal
NDC: 85464-002 | Form: SHAMPOO
Manufacturer: CAVTECH HOLDING LLC
Category: otc | Type: HUMAN OTC DRUG LABEL
Date: 20251222

ACTIVE INGREDIENTS: SALICYLIC ACID 3 g/100 g; ZINC PYRITHIONE 1 g/100 g
INACTIVE INGREDIENTS: WATER; TEA TREE OIL; ROSEMARY OIL; PEPPERMINT OIL

Initial Drug Listing - ProBliva Medicated Anti-Fungal Shampoo

ACTIVE INGREDIENT

Salicylic Acid 3%
Zinc Pyrithione 1%

PURPOSE

Anti-Seborheic Dermatitisand psoriasis, Anti-Dandruff

DOSAGE AND ADMINISTRATION

For the relief of flaking, and itching associated withdandruff, and seborrheic denatitis and to help prevent their recurrence.

WARNINGS

For external use only

ASK DOCTOR

condition covers a large area of the body

WHEN USING

- avoid contact with the eyes.lf contact occurs, rinseeyes thoroughly with water.
- for color-treated or pemmed hair, rinse thoroughly.

STOP USE

condition worsens or does not improve after regularuse of this product as directed.

Keep out of reach of children.

INDICATIONS AND USAGE

- shake well
- shampoo, then rinse thoroughly
- for best result, use at least twice a week or asdirected by a doctor

OTHER SAFETY INFORMATION

Store at room temperature

INACTIVE INGREDIENT

Water, Tea Tree Oil, Peppermint Oil, Rosemary Oil

QUESTIONS

Satisfaction guaranteed -For questions or comments,please contact.Seryice@ProBlivaBeauty.com